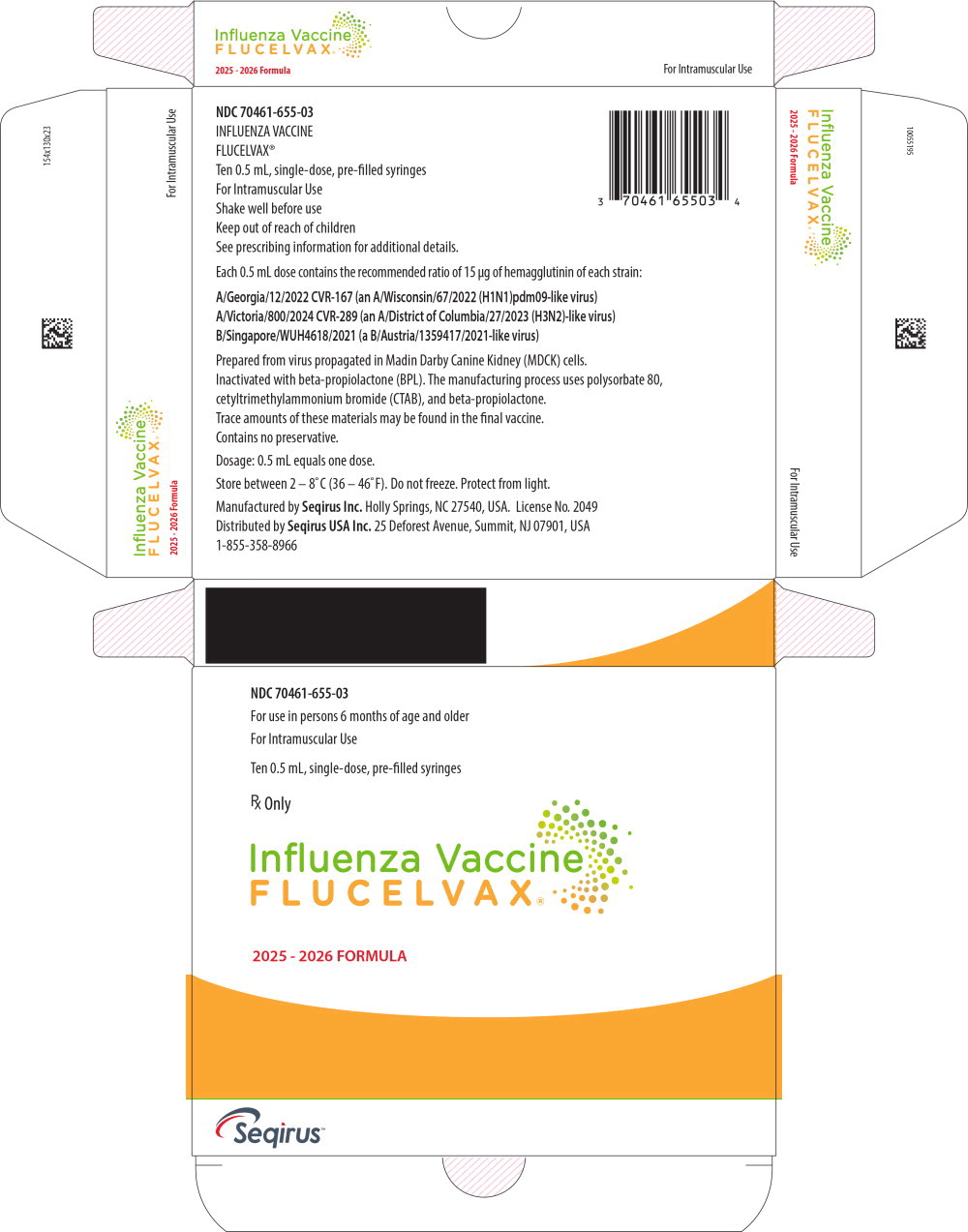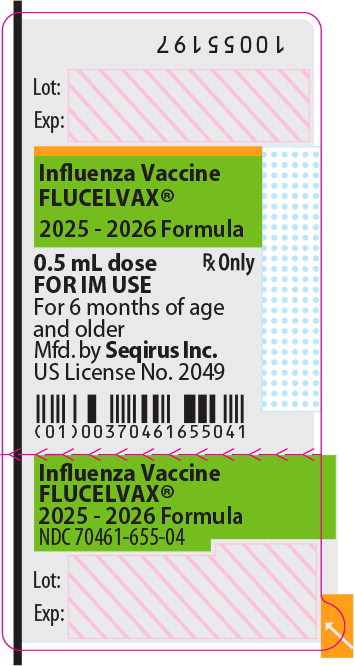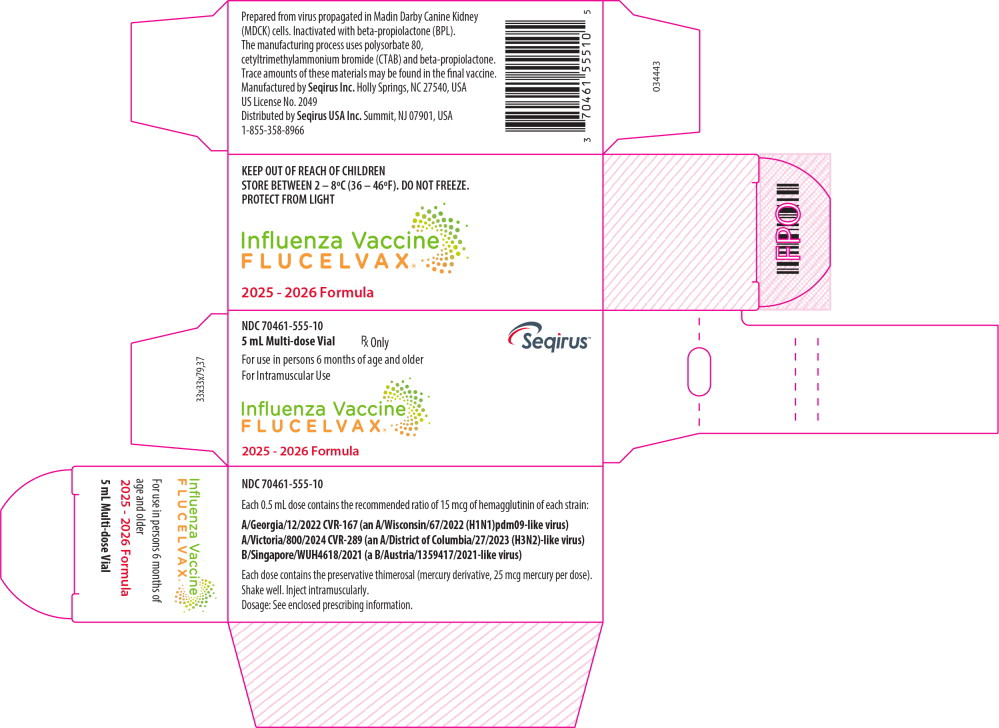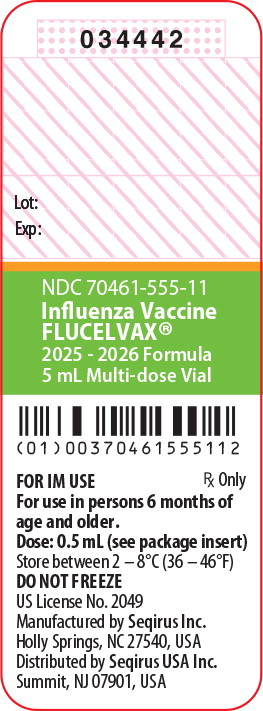 DRUG LABEL: Flucelvax
NDC: 70461-655 | Form: INJECTION, SUSPENSION
Manufacturer: Seqirus Inc.
Category: other | Type: VACCINE LABEL
Date: 20250701

ACTIVE INGREDIENTS: INFLUENZA A VIRUS A/Georgia/12/2022 CVR-167 (H1N1) ANTIGEN (MDCK CELL DERIVED, PROPIOLACTONE INACTIVATED) 15 ug/0.5 mL; INFLUENZA A VIRUS A/Victoria/800/2024 CVR-289 (H3N2) ANTIGEN (MDCK CELL DERIVED, PROPIOLACTONE INACTIVATED) 15 ug/0.5 mL; INFLUENZA B VIRUS B/Singapore/WUH4618/2021 ANTIGEN (MDCK CELL DERIVED, PROPIOLACTONE INACTIVATED) 15 ug/0.5 mL
INACTIVE INGREDIENTS: POTASSIUM CHLORIDE; SODIUM CHLORIDE; MAGNESIUM CHLORIDE; SODIUM PHOSPHATE, DIBASIC, DIHYDRATE; POTASSIUM PHOSPHATE, MONOBASIC; WATER

HIGHLIGHTS OF PRESCRIBING INFORMATION

These highlights do not include all the information needed to use FLUCELVAX® safely and effectively. See full prescribing information for FLUCELVAX.
FLUCELVAX (Influenza Vaccine)
Injectable Suspension, for Intramuscular Use
2025-2026 Formula
Initial U.S. Approval: 2012

1 INDICATIONS AND USAGE

FLUCELVAX is an inactivated vaccine indicated for active immunization for the prevention of influenza disease caused by influenza virus subtypes A and type B contained in the vaccine. (1)

FLUCELVAX is approved for use in persons 6 months of age and older. (1)

2 DOSAGE AND ADMINISTRATION

For intramuscular use.

Age | Dose | Schedule
6 months through 8 years of age | One or two dosesa, 0.5 mL each | If 2 doses, administer at least 4 weeks apart
9 years of age and older | One dose, 0.5 mL | Not Applicable
a 1 or 2 doses depends on vaccination history as per Advisory Committee on Immunization Practices annual recommendations on prevention and control of influenza with vaccines.

3 DOSAGE FORMS AND STRENGTHS

FLUCELVAX is an injectable suspension. A single dose is 0.5 mL (3)

4 CONTRAINDICATIONS

Do not administer FLUCELVAX to anyone with a history of a severe allergic reaction (e.g., anaphylaxis) to any component of the vaccine. (4, 11)

5 WARNINGS AND PRECAUTIONS

- If Guillain-Barré syndrome has occurred within 6 weeks of receipt of a prior influenza vaccine, the decision to give FLUCELVAX should be based on careful consideration of the potential benefits and risks. (5.1)

6 ADVERSE REACTIONS

Data for FLUCELVAX QUADRIVALENT are relevant to FLUCELVAX because both vaccines are manufactured using the same process and have overlapping compositions.

- In children 6 months through 3 years of age who received FLUCELVAX QUADRIVALENT, the most commonly reported injection-site adverse reactions were tenderness (28%), erythema (26%), induration (17%) and ecchymosis (11%). The most common systemic adverse reactions were irritability (28%), sleepiness (27%), diarrhea (18%) and change of eating habits (17%). (6)
- In children 4 through 8 years of age who received FLUCELVAX, the most commonly reported local injection-site adverse reactions were pain (29%) and erythema (11%). The most common systemic adverse reaction was fatigue (10%). (6)
- In children and adolescents 9 through 17 years of age who received FLUCELVAX, the most commonly reported injection-site adverse reactions were pain (34%) and erythema (14%). The most common systemic adverse reactions were myalgia (15%) and headache (14%). (6)
- In adults 18 through 64 years of age who received FLUCELVAX, the most commonly reported injection-site adverse reactions were pain (28%) and erythema (13%). The most common systemic adverse reactions were headache (16%), fatigue (12%), myalgia (11%) and malaise (10%). (6)
- In adults ≥65 years who received FLUCELVAX the most commonly reported injection-site reaction was erythema (10%). The most common systemic adverse reactions were fatigue (11%), headache (10%) and malaise (10%). (6)

To report SUSPECTED ADVERSE REACTIONS, contact Seqirus at 1-855-358-8966 or VAERS at 1-800-822-7967 or www.vaers.hhs.gov.

8 USE IN SPECIFIC POPULATIONS

- Geriatric Use: Antibody responses were lower in adults 65 years and older than in younger adults. (8.5)

FULL PRESCRIBING INFORMATION

1 INDICATIONS AND USAGE

FLUCELVAX is an inactivated vaccine indicated for active immunization for the prevention of influenza disease caused by influenza virus subtypes A and type B contained in the vaccine. FLUCELVAX is approved for use in persons 6 months of age and older. [see Clinical Studies (14)]

2 DOSAGE AND ADMINISTRATION

For intramuscular use.

2.1 Dosage and Schedule

Administer FLUCELVAX as a single 0.5 mL dose.

Table 1: Dosage and Schedule
Age | Dose | Schedule
6 months through 8 years of age | One or two doses^1, 0.5 mL each | If 2 doses, administer at least 4 weeks apart
9 years of age and older | One dose, 0.5 mL | Not Applicable
^1 1 or 2 doses depends on vaccination history as per Advisory Committee on Immunization Practices annual recommendations on prevention and control of influenza with vaccines.

2.2 Administration

Shake the syringe vigorously before administering and shake the multi-dose vial preparation each time before withdrawing a dose of vaccine. FLUCELVAX is a slightly opalescent suspension. Parenteral drug products should be inspected visually for particulate matter and discoloration prior to administration whenever solution and container permit. If either condition exists, do not administer the vaccine. Between uses, return the multi-dose vial to the recommended storage conditions between 2º and 8ºC (36º and 46ºF). Do not freeze. Discard if the vaccine has been frozen.

Administer FLUCELVAX intramuscularly.

3 DOSAGE FORMS AND STRENGTHS

FLUCELVAX is an injectable suspension. A single dose is 0.5 mL.

4 CONTRAINDICATIONS

Do not administer FLUCELVAX to anyone with a history of a severe allergic reaction (e.g., anaphylaxis) to any component of the vaccine [see Description (11)].

5 WARNINGS AND PRECAUTIONS

5.1 Guillain-Barré Syndrome

If Guillain-Barré syndrome (GBS) has occurred after receipt of a prior influenza vaccine, the decision to give FLUCELVAX should be based on careful consideration of the potential benefits and risks.

The 1976 swine influenza vaccine was associated with an elevated risk of GBS. Evidence for a causal relation of GBS with other influenza vaccines is inconclusive; if an excess risk exists, it is probably slightly more than 1 additional case per 1 million persons vaccinated.^1

5.2 Preventing and Managing Allergic Reactions

Appropriate medical treatment must be immediately available to manage potential anaphylactic reactions following administration of FLUCELVAX.

5.3 Syncope

Syncope (fainting) has been reported following vaccination with FLUCELVAX. Procedures should be in place to avoid injury from fainting.

5.4 Altered Immunocompetence

After vaccination with FLUCELVAX, immunocompromised individuals, including those receiving immunosuppressive therapy, may have a reduced immune response.

5.5 Limitations of Vaccine Effectiveness

Vaccination with FLUCELVAX may not protect all vaccine recipients against influenza disease.

6 ADVERSE REACTIONS

Data for FLUCELVAX QUADRIVALENT are relevant to FLUCELVAX because both vaccines are manufactured using the same process and have overlapping compositions.

In children 6 months through 3 years of age who received FLUCELVAX QUADRIVALENT, the most commonly reported (≥10%) injection-site adverse reactions were tenderness (28%), erythema (26%), induration (17%) and ecchymosis (11%). The most common systemic adverse reactions were irritability (28%), sleepiness (27%), diarrhea (18%) and change of eating habits (17%).

In children 4 through 8 years of age who received FLUCELVAX, the most commonly reported (≥10%) local injection-site adverse reactions were pain (29%) and erythema (11%). The most common systemic adverse reaction was fatigue (10%).

In children and adolescents 9 through 17 years of age who received FLUCELVAX, the most commonly reported (≥10%) injection-site adverse reactions were pain (34%) and erythema (14%). The most common systemic adverse reactions were myalgia (15%) and headache (14%).

In adults 18 through 64 years of age who received FLUCELVAX, the most commonly reported (≥10%) injection-site adverse reactions were pain (28%) and erythema (13%). The most common systemic adverse reactions were headache (16%), fatigue (12%), myalgia (11%) and malaise (10%).

In adults 65 years of age and older who received FLUCELVAX the most commonly reported (≥10%) injection-site reaction was erythema (10%). The most common systemic adverse reactions were fatigue (11%), headache (10%) and malaise (10%).

6.1 Clinical Trials Experience

Because clinical studies are conducted under widely varying conditions, adverse reaction rates observed in the clinical studies of a vaccine cannot be directly compared to rates in clinical studies of another vaccine and may not reflect rates observed in clinical practice.

Children and Adolescents 6 months through 17 years of age:

Study 1 (NCT 04074928) was a randomized, observer-blind, multicenter study in children 6 months through 3 years of age. The safety population included a total of 2402 children 6 months through 3 years of age who received FLUCELVAX QUADRIVALENT (N=1597) or a US-licensed quadrivalent influenza vaccine comparator, AFLURIA QUADRIVALENT (N=805). In the safety population, 894 subjects (37.2%) were 6 months through 23 months of age, and 1508 subjects (62.8%) were 24 months through 47 months of age. The solicited safety set consisted of 2348 subjects who received FLUCELVAX QUADRIVALENT (N=1564) or a US-licensed quadrivalent influenza vaccine comparator (N=784). Study subjects received one or two doses (separated by 4 weeks) of FLUCELVAX QUADRIVALENT or the comparator vaccine depending on the subject's prior influenza vaccination history. Data for FLUCELVAX QUADRIVALENT are relevant to FLUCELVAX because both vaccines are manufactured using the same process and have overlapping compositions.

In this study, solicited local injection site and systemic adverse reactions were collected on a symptom diary card for 7 days following vaccination.

In children 6 months through 3 years of age, the incidence of local and systemic solicited adverse reactions reported by children who received FLUCELVAX QUADRIVALENT and comparator are summarized in Table 2.

Table 2: Incidence of Solicited Adverse Reactions in the Safety Population^1 (6 months through 3 years of age) Reported Within 7 Days of Any Dose of Vaccination (Study 1)
 | Percentage (%)^2 of participants Reporting a Reaction
 | Participants 6 through 23 months |  |  |  | Participants 24 through 47 months
 | FLUCELVAX QUADRIVALENT N=581 |  | Comparator^3 N=292 |  | FLUCELVAX QUADRIVALENT N=983 |  | Comparator^3 N=492
 | Any | Gr 3 | Any | Gr 3 | Any | Gr 3 | Any | Gr 3
Local Adverse Reactions^4
Tenderness | 25.5 | 2.1 | 23.3 | 1.4 | 29.3 | 2.2 | 33.9 | 1.4
Erythema | 25.3 | 0 | 18.2 | 0 | 26.0 | 0.7 | 28.5 | 0
Induration | 16.5 | 0.5 | 12.0 | 0 | 17.7 | 0.3 | 18.3 | 0
Ecchymosis | 11.2 | 0.2 | 7.5 | 0 | 10.5 | 0.1 | 12.8 | 0
Systemic Adverse Reactions^5
Irritability | 35.1 | 5.2 | 35.6 | 2.1 | 23.6 | 1.8 | 26.0 | 3.0
Sleepiness | 35.5 | 2.4 | 30.5 | 1.7 | 21.8 | 1.9 | 22.6 | 1.2
Diarrhea | 23.2 | 2.4 | 20.2 | 0.7 | 14.8 | 1.1 | 14.0 | 1.2
Change of eating habits | 21.0 | 1.7 | 21.9 | 2.4 | 15.3 | 1.4 | 15.0 | 1.2
Fever | 9.3 | 0.7 | 10.3 | 0 | 5.4 | 0.6 | 4.8 | 0.2
Vomiting | 10.5 | 0.7 | 6.8 | 0.7 | 4.6 | 0.5 | 5.9 | 0.4
Shivering | 3.1 | 0.2 | 3.1 | 0 | 3.3 | 0.2 | 3.7 | 0
Abbreviations: Gr 3, Grade 3.
N = number of participants in the Safety Population for each study vaccine group.
^1 Solicited Safety Population: participants who were vaccinated and provided any solicited local or systemic adverse reaction safety data on subject diary cards from Day 1 through Day 7 after vaccination.
^2 Proportion of participants reporting each solicited local adverse reaction or systemic adverse event by study vaccine group based on the number of participants contributing any follow up safety information for at least one data value of an individual sign/symptom.
^3 Comparator: US-Licensed Quadrivalent Influenza vaccine
^4 Local adverse reactions: Grade 3 tenderness defined as, “Cried when limb was moved/spontaneously painful” in subjects 6 through 23 months, and “Prevents daily activity” in subjects 24 months and older; Erythema, induration and ecchymosis: any = ≥1mm diameter, Grade 3 => 50 mm diameter.
^5 Systemic adverse reactions: Fever: any = ≥ 100.4°F , Grade 3 = ≥ 104.0°F (either rectal, oral, axillary, or tympanic membrane); Grade 3 change of eating habits: Missed more than 2 feeds/meals; Grade 3 sleepiness: Sleeps most of the time and is hard to arouse him/her; Grade 3 vomiting: 6 or more times in 24 hours or requires intravenous hydration; Grade 3 diarrhea: 6 or more loose stools in 24 hours or requires intravenous hydration; Grade 3 irritability: unable to console. Grade 3 for all other adverse reactions is that which prevents daily activity.
The rates of antipyretic or analgesic use reported on the diary card for prophylaxis or treatment of high temperature or pain were as follows: 6 through 23 months of age FLUCELVAX QUADRIVALENT 20.3%, Comparator 23.6%; 24 through 47 months of age FLUCELVAX QUADRIVALENT 12.4%, Comparator 13.6%.
Study 1: NCT 04074928

In children who received two doses, the rates of solicited local and systemic adverse reactions were generally similar or lower after the second dose compared to the first dose.

All unsolicited adverse events were collected for 28 days after last vaccination. In children 6 months through 3 years of age, unsolicited adverse events were reported in 26.2% of subjects who received FLUCELVAX QUADRIVALENT and 25.7% of subjects who received the US-licensed quadrivalent influenza vaccine comparator within 28 days after last vaccination.

In children 6 months through 3 years of age, serious adverse events (SAEs) were collected throughout the study duration (until 6 months after last vaccination) and were reported by 0.9% of the subjects who received FLUCELVAX QUADRIVALENT and 0.9% of subjects who received the US-licensed quadrivalent influenza vaccine comparator. None of the SAEs were assessed as being related to study vaccine.

Information on the safety of FLUCELVAX administered to 3346 children and adolescents 4 through 17 years of age is available from two multinational, randomized, controlled clinical studies (Studies 2- NCT 00645411 and 3- NCT 01857206). In both studies, children 9 through 17 years of age received a single dose of FLUCELVAX or a US-licensed trivalent inactivated influenza vaccine (FLUVIRIN). In study 2, all children 4 through 8 years of age received two doses of study vaccine separated by 4 weeks. In study 3, children 4 through 8 years of age received one or two doses (separated by 4 weeks) of study vaccine based on determination of the subject's prior influenza vaccination history. Among subjects enrolled in these two studies, the mean age was 8.5 years, 49% were female, and 59% were Caucasian.

Solicited adverse reactions for FLUCELVAX and the comparator trivalent influenza vaccine (FLUVIRIN) for study 2 are summarized in Table 3. In children who received a second dose of FLUCELVAX or the comparator trivalent influenza vaccine (FLUVIRIN), the incidence of adverse reactions following the second dose of vaccine were similar to those observed with the first dose.

Table 3: Solicited Adverse Reactions in the Safety Population^1 Reported Within 7 Days of Vaccination with FLUCELVAX (Study 2^2)
 | Children 4 through 8 Years
Adverse Reaction | Percentages (%)^3
Adverse Reaction | FLUCELVAX N=1324 |  |  | Comparator^4 N=831
Adverse Reaction | Any | Moderate^5 | Severe^5 | Any | Moderate^5 | Severe^5
Local adverse reactions
Injection site pain | 29 | 4 | <1 | 26 | 3 | 1
Erythema | 11 | <1 | 0 | 14 | 0 | 0
Induration | 6 | <1 | 0 | 4 | 0 | 0
Swelling | 4 | 0 | 0 | 5 | <1 | 0
Ecchymosis | 6 | 0 | 0 | 6 | 0 | 0
Systemic adverse reactions
Headache | 9 | 2 | 1 | 11 | 3 | <1
Fatigue | 10 | 2 | <1 | 12 | 2 | 1
Myalgia | 9 | 2 | <1 | 8 | 2 | <1
Malaise | 7 | 2 | 1 | 8 | 2 | 1
Chills | 3 | <1 | <1 | 5 | 1 | <1
Arthralgia | 3 | <1 | 0 | 1 | <1 | 0
Sweating | 2 | <1 | <1 | 2 | 1 | <1
Fever ≥38°C | 2 | 1 | <1 | 4 | 1 | 0
Adverse Reaction | Children and Adolescents 9 through 17 Years
Adverse Reaction | Percentages (%)
Adverse Reaction | FLUCELVAX N=652 |  |  | Comparator^4 N=316
Adverse Reaction | Any | Moderate^5 | Severe^5 | Any | Moderate^5 | Severe^5
Local adverse reactions
Injection site pain | 34 | 5 | <1 | 38 | 9 | 1
Erythema | 14 | 0 | 0 | 14 | <1 | 0
Induration | 7 | <1 | 0 | 9 | 0 | 0
Swelling | 5 | <1 | 0 | 5 | <1 | 0
Ecchymosis | 5 | 0 | 0 | 3 | 0 | 0
Systemic adverse reactions
Headache | 14 | 3 | <1 | 14 | 5 | 1
Fatigue | 9 | 2 | 1 | 13 | 3 | 1
Myalgia | 15 | 3 | <1 | 19 | 4 | 1
Malaise | 9 | 2 | 1 | 11 | 3 | 1
Chills | 4 | 1 | <1 | 4 | <1 | <1
Arthralgia | 4 | <1 | <1 | 5 | 1 | 0
Sweating | 2 | 0 | 0 | 1 | 0 | <1
Fever ≥38°C | 1 | <1 | 0 | 1 | 0 | 0
^1 Safety population: all subjects in the exposed population who provided post-vaccination safety data.
^2 NCT 00645411
^3 For children 4 through 8 years of age, data shown are after first dose of vaccination
^4 FLUVIRIN (Influenza Virus Vaccine)
^5 Severity gradings: For erythema, induration, ecchymosis and swelling: Moderate= 51-≤100 mm; Severe= >100 mm; For pain and systemic adverse reactions: Moderate = some limitation to perform daily activity; Severe = unable to perform daily activity; For fever: Moderate = 39-<40°C; Severe = ≥40°C

In studies 2 and 3 combined, the frequencies of unsolicited non-serious adverse events occurring within 28 days of vaccination were present in 32% of subjects who received FLUCELVAX and in 35% of subjects who received a comparator trivalent inactivated influenza vaccine.

One case of erythema multiforme considered related to vaccination with FLUCELVAX occurred in a 5 year old male.

In the two controlled studies in children and adolescents 4 through 17 years of age, serious adverse events were monitored for 6 months after last vaccination. Serious adverse events occurring within 28 days of any vaccination were reported in <1% of subjects (8 of 3345) who received FLUCELVAX, and in <1% of subjects (5 of 1828) who received a comparator trivalent influenza vaccine . No serious adverse events occurring within 6 months post-vaccination were considered related to the study vaccine.

Additional safety data are available from Study 4 (NCT 03165617). Study 4 was a multi-season, multi-national (Australia, Estonia, Finland, Lithuania, Philippines, Poland, Spain, Thailand), randomized, observer-blind study in children and adolescents 2 through 17 years of age. The solicited safety population included a total of 4509 children and adolescents 2 through 17 years of age who received FLUCELVAX QUADRIVALENT (N=2255) or a non-influenza (meningococcal (Groups A, C, Y, and W-135) oligosaccharide diphtheria CRM197 conjugate) comparator vaccine (N=2254).

Children 2 through 8 years of age received one or two doses (separated by 4 weeks) of FLUCELVAX QUADRIVALENT or comparator vaccine depending on the subject's prior influenza vaccination history. Children in the 2-dose comparator group received non-influenza comparator as the first dose and saline placebo as the second dose. Children and adolescents 9 through 17 years of age received a single dose of FLUCELVAX QUADRIVALENT or non-influenza comparator vaccine.

In this study, serious adverse events (SAEs) were collected throughout the study duration (until 6 months after last vaccination) and were reported by 1.1% of the children and adolescents who received FLUCELVAX QUADRIVALENT. None of the SAEs were assessed as being related to study vaccine.

Adults 18 years of age and older:

The safety of FLUCELVAX was evaluated in seven randomized, controlled studies conducted in the US, Europe and New Zealand (Study 5: NCT 00630331, Study 6: NCT 00492063, Study 7: NCT 00306527, Study 8: NCT 00264576, Study 9: NCT 00310804, Study 10: NCT number not assigned, Study 11: NCT number not assigned). The safety population includes 5709 adults 18 through 64 years of age and 572 adults 65 years of age and older administered FLUCELVAX.

In all studies, solicited local injection site and systemic adverse reactions were collected from subjects who completed a symptom diary card for 7 days following vaccination.

One of the seven clinical trials, Study 5 (NCT 00630331) was a randomized, double-blind, placebo-controlled study that evaluated three vaccines including: FLUCELVAX (N=3813), placebo (N=3894) and another influenza vaccine. The population was 18 through 49 years of age (mean 32.8 years), 55% were female and 84% were Caucasian. Solicited adverse reactions for FLUCELVAX and placebo are summarized in Table 4.

Table 4: Solicited Adverse Reactions in the Safety Population^2 Reported Within 7 Days of Vaccination with FLUCELVAX (Study 5^1)
 | Adults 18 through 49 Years
 | Percentages (%)
 | FLUCELVAX N=3813 | Placebo^3 N=3894
Local adverse reactions
Injection site pain | 30 | 10
Erythema | 13 | 10
Induration | 6 | 3
Swelling | 6 | 3
Ecchymosis | 4 | 4
Systemic adverse reactions
Headache | 15 | 15
Fatigue | 10 | 10
Myalgia | 12 | 7
Malaise | 8 | 6
Chills | 6 | 6
Arthralgia | 3 | 3
Sweating | 3 | 3
Fever (≥38o C) | 1 | <1
^1 NCT 00630331
^2 Safety population: all subjects in the exposed population who provided post vaccination safety data.
^3 Placebo: 0.5 mL Phosphate Buffered Saline

Study 6 (NCT 00492063) was a randomized, double-blind study comparing FLUCELVAX (N=1330) to AGRIFLU, a US-licensed trivalent inactivated influenza vaccine (N=1324) in adults 18 years of age or older. The mean age was 43.7 years of age for adults 18 through 64 years of age and 71.3 years of age for adults 65 years of age and older; 57% of subjects were female and 100% were Caucasian. The safety data observed are summarized in Table 5.

Table 5: Solicited Adverse Reactions in the Safety Population^1 Reported Within 7 Days of Vaccination with FLUCELVAX (Study 6^2)
 | Adults 18 through 64 Years |  | Adults 65 Years of Age and Older
 | Percentages (%)
 | FLUCELVAX N=821 | Comparator^3 N=841 | FLUCELVAX N=509 | Comparator^3 N=483
Local adverse reactions
Injection site pain | 20 | 15 | 8 | 4
Erythema | 14 | 15 | 10 | 11
Induration | 6 | 6 | 5 | 4
Swelling | 4 | 4 | 4 | 2
Ecchymosis | 3 | 3 | 4 | 4
Systemic adverse reactions
Headache | 12 | 11 | 10 | 11
Fatigue | 11 | 11 | 11 | 13
Myalgia | 7 | 8 | 6 | 8
Malaise | 11 | 11 | 10 | 11
Chills | 4 | 4 | 3 | 4
Arthralgia | 5 | 5 | 6 | 7
Sweating | 5 | 4 | 7 | 8
Fever (≥38o C) | 1 | 1 | <1 | 1
^1 Safety population: all subjects in the exposed population who provided post-vaccination safety data.
^2 NCT 00492063
^3 AGRIFLU (Influenza Virus Vaccine)

Unsolicited adverse events, including serious adverse events (SAEs), were collected for 21 days after vaccination in five studies. In adults 18 through 64 years of age (N=4038), 13% (284 out of 2266) of subjects who received FLUCELVAX and 13% (224 out of 1772) of subjects who received the comparator trivalent influenza vaccine (AGRIFLU) reported at least one unsolicited adverse event within 21 days after vaccination. The most commonly reported unsolicited adverse events after FLUCELVAX vaccination were rhinitis (3%), headache (2%) and oropharyngeal pain (2%). In adults 65 years of age and older (N=2013), 11% (110 out of 997) of subjects who received FLUCELVAX and 9% (95 out of 1016) of subjects who received the comparator trivalent influenza vaccine (AGRIFLU) reported at least one unsolicited adverse event within 21 days after vaccination. Within this age group, the most commonly reported unsolicited adverse events after FLUCELVAX vaccination were rhinitis (3%) and cough (2%). In both age groups, all other unsolicited adverse events were reported in 1% or fewer subjects.

In the seven controlled studies of FLUCELVAX, serious adverse events were collected for a duration of 21 days in two studies and for a duration of 6 to 9 months in five studies. Participants in Study 6 were revaccinated with FLUCELVAX or AGRIFLU in Study 7. Across the seven controlled studies, the rates per dose of serious adverse events among adults 18 through 64 years of age were 1% (84 out of 6388 doses) for FLUCELVAX, 1% (55 out of 5745 doses) for the comparator trivalent influenza vaccine (AGRIFLU) and 1% (37 out of 3894 doses) for placebo. The rates per dose of serious adverse events among adults 65 years of age and older were 4% (36 out of 997 doses) for FLUCELVAX and 4% (44 out of 1016 doses) for the comparator trivalent influenza vaccine (AGRIFLU).

6.2 Postmarketing Experience

The following additional adverse events have been identified during post-approval use of FLUCELVAX or FLUCELVAX QUADRIVALENT. Because these events are reported voluntarily from a population of uncertain size, it is not always possible to reliably estimate their frequency or establish a causal relationship to the vaccine.

Immune system disorders: Allergic or immediate hypersensitivity reactions, including anaphylactic shock.

Nervous systems disorders: Syncope, presyncope, paresthesia, Guillain-Barré syndrome.

Skin and subcutaneous tissue disorders: Generalized skin reactions including pruritus, urticaria or non-specific rash.

General disorders and administration site conditions: Extensive swelling of injected limb.

8 USE IN SPECIFIC POPULATIONS

8.1 Pregnancy

Risk Summary

All pregnancies have a risk of birth defect, loss, or other adverse outcomes. In the US general population, the estimated background risk of major birth defects and miscarriage in clinically recognized pregnancies is 2% to 4% and 15% to 20%, respectively. Data collected in a prospective Pregnancy Exposure Registry from 665 women vaccinated with FLUCELVAX QUADRIVALENT showed no evidence of a vaccine-associated increase in the risk of major birth defects and miscarriages when FLUCELVAX QUADRIVALENT is administered during any trimester of pregnancy (see Data). Data for FLUCELVAX QUADRIVALENT are relevant to FLUCELVAX because both vaccines are manufactured using the same process and have overlapping compositions.

A developmental toxicity study has been performed in female rabbits administered FLUCELVAX prior to mating and during gestation. The dose was 0.5 mL on each occasion (a single human dose is 0.5 mL). This study revealed no evidence of harm to the fetus due to FLUCELVAX.

Clinical Considerations

Disease-associated Maternal and/or Embryo-Fetal Risk

Pregnant women are at increased risk for severe illness due to influenza compared to non-pregnant women. Pregnant women with influenza may be at increased risk for adverse pregnancy outcomes, including preterm labor and delivery.

Data

Human Data

Data from a prospective Pregnancy Exposure Registry in the US were collected from women vaccinated with FLUCELVAX QUADRIVALENT during 3 Northern Hemisphere influenza seasons (2017-18 through 2019-20) and there was no evidence of a vaccine-associated increase in the risk of major birth defects and miscarriages. A total of 665 pregnancy outcomes were reported, of which 27%, 42%, and 31% of the pregnancies were exposed to FLUCELVAX QUADRIVALENT during the 1st, 2nd, and 3rd trimester, respectively; 659 resulted in live births, 4 resulted in spontaneous pregnancy loss, 1 resulted in ectopic pregnancy, 1 resulted in elective pregnancy termination and there were no stillbirths. The prevalence rates for miscarriage and major birth defects assessed at time of birth were each 1.9% from the study. These rates of assessed outcomes in the prospective population were consistent with estimated background rates.

Animal Data

In a developmental toxicity study, female rabbits were administered FLUCELVAX by intramuscular injection 1, 3, and 5 weeks prior to mating, and on gestation days 7 and 20. The dose was 0.5 mL on each occasion (a single human dose is 0.5 mL). No vaccine-related fetal malformations or variations and no adverse effects on pre-weaning development or on female fertility were observed in the study.

8.2 Lactation

Risk Summary

It is not known whether FLUCELVAX is excreted in human milk. Data are not available to assess the effects of FLUCELVAX on the breastfed infant or on milk production/excretion.

The developmental and health benefits of breastfeeding should be considered along with the mother's clinical need for FLUCELVAX and any potential adverse effects on the breastfed child from FLUCELVAX or from the underlying maternal condition. For preventive vaccines, the underlying maternal condition is susceptibility to disease prevented by the vaccine or the effects on milk production.

8.4 Pediatric Use

Safety and effectiveness have not been established in children less than 6 months of age.

8.5 Geriatric Use

Of the total number of subjects who received one dose of FLUCELVAX in clinical studies and included in the safety population (6281), 9% (572) were 65 years of age and older and 2% (140) were 75 years of age or older.

Antibody responses to FLUCELVAX were lower in the geriatric (adults 65 years and older) population than in younger adults.

11 DESCRIPTION

FLUCELVAX (Influenza Vaccine) is a trivalent subunit influenza vaccine manufactured using cell derived candidate vaccine viruses (CVV) that are propagated in Madin Darby Canine Kidney (MDCK) cells, a continuous cell line. These cells were adapted to grow freely in suspension in culture medium. The virus is inactivated with β-propiolactone, disrupted by the detergent cetyltrimethylammonium bromide and purified through several process steps. Each of the virus strains are produced and purified separately then pooled to formulate the vaccine.

FLUCELVAX is a sterile, slightly opalescent injectable suspension in phosphate buffered saline. FLUCELVAX is standardized according to United States Public Health Service requirements for the 2025-2026 influenza season and is formulated to contain a total of 45 micrograms (mcg) hemagglutinin (HA) per 0.5 mL dose in the recommended ratio of 15 mcg HA of each of the following influenza strains:

A/Georgia/12/2022 CVR-167 (an A/Wisconsin/67/2022 (H1N1)pdm09-like virus);

A/Victoria/800/2024 CVR-289(an A/District of Columbia/27/2023 (H3N2)-like virus);

B/Singapore/WUH4618/2021 (a B/Austria/1359417/2021-like virus).

Each dose of FLUCELVAX may contain residual amounts of MDCK cell protein (≤ 21.6 mcg), protein other than HA (≤ 225 mcg), MDCK cell DNA (≤ 10 ng), polysorbate 80 (≤ 1125 mcg), cetyltrimethylammonium bromide (≤ 13.5 mcg), and β-propiolactone (< 0.5 mcg), which are used in the manufacturing process.

FLUCELVAX contains no egg protein or antibiotics.

FLUCELVAX 0.5 mL pre-filled syringes contain no preservative.

FLUCELVAX 5 mL multi-dose vials contain thimerosal, a mercury derivative, added as a preservative. Each 0.5 mL dose from the multi-dose vial contains 25 mcg mercury.

The tip caps and plungers of the pre-filled syringes and the multi-dose vial stopper are not made with natural rubber latex.

12 CLINICAL PHARMACOLOGY

12.1 Mechanism of Action

Specific levels of hemagglutination inhibition (HI) antibody titers induced by vaccination with inactivated influenza virus vaccine have not been correlated with protection from influenza illness. In some studies, HI antibody titers of ≥ 1:40 have been associated with protection from influenza illness in up to 50% of adults.^2,3

Antibody against one influenza virus type or subtype confers little or no protection against another. Furthermore, antibody to one antigenic variant of influenza virus might not protect against a new antigenic variant of the same type or subtype. Frequent development of antigenic variants through antigenic drift is the virologic basis for seasonal epidemics and the reason for the usual change of one or more strains in each year's influenza vaccine.

13 NONCLINICAL TOXICOLOGY

13.1 Carcinogenesis, Mutagenesis, Impairment of Fertility

FLUCELVAX has not been evaluated for carcinogenic or mutagenic potential, or for impairment of male fertility in animals.

14 CLINICAL STUDIES

14.1 Efficacy in Adults

A multinational (US, Finland, and Poland), randomized, observer-blind, placebo-controlled trial was performed to assess clinical efficacy and safety of FLUCELVAX during the 2007-2008 influenza season in adults aged 18 through 49 years (Study 5). A total of 11,404 adults were enrolled to receive FLUCELVAX (N=3828), AGRIFLU (N=3676) or placebo (N=3900) in a 1:1:1 ratio. Among the overall study population enrolled, the mean age was 33 years, 55% were female, 84% were Caucasian, 7% were Black, 7% were Hispanic, and 2% were of other ethnic origin.

FLUCELVAX efficacy was assessed by the prevention of culture-confirmed symptomatic influenza illness caused by viruses antigenically matched to those in the vaccine and prevention of influenza illness caused by all influenza viruses compared to placebo. Influenza cases were identified by active and passive surveillance of influenza-like illness (ILI). ILI was defined as a fever (oral temperature ≥ 100.0°F / 38°C) and cough or sore throat. Nose and throat swab samples were collected for analysis within 120 hours of onset of an influenza-like illness in the period from 21 days to 6 months after vaccination. Overall vaccine efficacy against all influenza viral subtypes and vaccine efficacy against individual influenza viral subtypes were calculated (Tables 6 and 7, respectively).

Table 6: Vaccine Efficacy against Culture-Confirmed Influenza in Participants aged 18 through 49 years (Study 5)
 | Number of participants per protocol | Number of participants with influenza | Attack Rate (%) | Vaccine Efficacy (VE)^1,2
 | Number of participants per protocol | Number of participants with influenza | Attack Rate (%) | % | Lower Limit of One- Sided 97.5% CI of VE^2,3
Antigenically Matched Strains
FLUCELVAX | 3776 | 7 | 0.19 | 83.8 | 61.0
Placebo | 3843 | 44 | 1.14 | -- | --
All Culture-Confirmed Influenza
FLUCELVAX | 3776 | 42 | 1.11 | 69.5 | 55.0
Placebo | 3843 | 140 | 3.64 | -- | --
^1 Efficacy against influenza was evaluated over a 9-month period in 2007/2008
^2 Simultaneous one-sided 97.5% confidence intervals for the vaccine efficacy (VE) of FLUCELVAX relative to placebo based on the Sidak-corrected score confidence intervals for the relative risk. Vaccine Efficacy = (1 - Relative Risk) x 100 %
^3 VE success criterion: the lower limit of the one-sided 97.5% CI for the estimate of the VE relative to placebo is > 40%
Study 5: NCT00630331

Table 7: Efficacy of FLUCELVAX against Culture-Confirmed Influenza by Influenza Viral Subtype in Participants aged 18 through 49 years (Study 5)
 | FLUCELVAX (N=3776) |  | Placebo (N=3843) |  | Vaccine Efficacy (VE)^2
 | Attack Rate (%) | Number of Participants with Influenza | Attack Rate (%) | Number of Participants with Influenza | % | Lower Limit of One-Sided 97.5% CI of VE^1,2
Antigenically Matched Strains
A/H3N2^3 | 0. 05 | 2 | 0 | 0 | -- | --
A/H1N1 | 0.13 | 5 | 1.12 | 43 | 88.2 | 67.4
B^3 | 0 | 0 | 0.03 | 1 | -- | --
All Culture-Confirmed Influenza
A/H3N2 | 0.16 | 6 | 0.65 | 25 | 75.6 | 35.1
A/H1N1 | 0.16 | 6 | 1.48 | 57 | 89.3 | 73.0
B | 0.79 | 30 | 1.59 | 61 | 49.9 | 18.2
^1 No VE success criterion was prespecified in the protocol for each individual influenza virus subtype.
^2 Simultaneous one-sided 97.5% confidence intervals for the vaccine efficacy (VE) of FLUCELVAX relative to placebo based on the Sidak-corrected score confidence intervals for the relative risk. Vaccine Efficacy = (1 - Relative Risk) x 100 %.
^3 There were too few cases of influenza due to vaccine-matched influenza A/H3N2 or B to adequately assess vaccine efficacy.
Study 5: NCT00630331

14.2 Efficacy in Children and Adolescents

Absolute efficacy of FLUCELVAX QUADRIVALENT was evaluated in children and adolescents 2 through 17 years of age in Study 4. This was a multinational, randomized, non-influenza vaccine comparator-controlled efficacy, immunogenicity and safety study conducted in 8 countries during the following 3 influenza seasons: Southern Hemisphere 2017, Northern Hemisphere 2017/2018 and Northern Hemisphere 2018/2019. The study enrolled 4514 children and adolescents. Out of the 4514 enrolled, 4513 received either FLUCELVAX QUADRIVALENT (N=2258) or a non-influenza (meningococcal (Groups A, C, Y, and W-135) oligosaccharide diphtheria CRM197 conjugate) comparator vaccine (N=2255). The full analysis set (FAS) for efficacy consisted of 4509 children and adolescents. Data for FLUCELVAX QUADRIVALENT are relevant to FLUCELVAX because both vaccines are manufactured using the same process and have overlapping compositions.

Children 2 through 8 years of age received either one or two doses (separated by 4 weeks) of FLUCELVAX QUADRIVALENT or comparator vaccine depending on the subject's prior influenza vaccination history. Children in the 2-dose comparator group received non-influenza comparator as the first dose and saline placebo as the second dose. Children and adolescents 9 through 17 years of age received a single dose of FLUCELVAX QUADRIVALENT or non-influenza comparator vaccine. Among all enrolled children and adolescents (N=4514), the mean age was 8.8 years, 48% were female, 51% were 2 through 8 years of age, 50% were Caucasian and 49% were Asian. There were no notable differences in the distribution of demographic and baseline characteristics between the two treatment groups.

FLUCELVAX QUADRIVALENT efficacy was assessed by the prevention of confirmed influenza illness caused by any influenza Type A or B strain. Influenza cases were identified by active and passive surveillance of influenza-like illness (ILI) and confirmed by cell culture and/or real-time polymerase chain reaction (RT-PCR). ILI was defined as a fever (oral temperature ≥ 100.0°F / 37.8°C) along with any of the following: cough, sore throat, nasal congestion, or rhinorrhea. The overall vaccine efficacy for the entire study population (2 through 17 years) was 54.6% (95% CI 45.7 – 62.1), which met predefined success criteria. In addition, vaccine efficacy was 50.5% (95% CI 38.4 – 60.2) in children 2 through 8 years of age and 61.9% (95% CI 47.4 – 72.3) in those 9 through 17 years of age. Vaccine efficacy against all influenza viral subtypes and against individual influenza viral subtypes antigenically similar to the subtypes in the vaccine were calculated (Table 8).

Table 8: Efficacy of FLUCELVAX QUADRIVALENT Against First Occurrence RT-PCR Confirmed or Culture Confirmed Influenza in Participants 2 through 17 years of age – FAS Efficacy^1 (Study 4).
 | Number of participants per protocol^1 | Number of cases of influenza | Attack Rate (%) | Vaccine Efficacy (VE)^2
 | Number of participants per protocol^1 | Number of cases of influenza | Attack Rate (%) | VE % | 95% Confidence Interval^3
RT-PCR or Culture Confirmed Influenza
FLUCELVAX QUADRIVALENT | 2257 | 175 | 7.8 | 54.6 | 45.7 - 62.1
Non-Influenza Comparator^4 | 2252 | 364 | 16.2 | - | -
Culture Confirmed Influenza
FLUCELVAX QUADRIVALENT | 2257 | 115 | 5.1 | 60.8 | 51.3 - 68.5
Non-Influenza Comparator^4 | 2252 | 279 | 12.4 | - | -
Antigenically Matched Culture-Confirmed Influenza
FLUCELVAX QUADRIVALENT | 2257 | 90 | 4.0 | 63.6 | 53.6 - 71.5
Non-Influenza Comparator^4 | 2252 | 236 | 10.5 | - | -
^1 Number of participants in the Full-Analysis Set (FAS) – Efficacy, which included all participants randomized, received a study vaccination and provided efficacy data
^2 Efficacy against influenza was evaluated over three influenza seasons, SH 2017, NH 2017-18 and NH 2018-19
^3 FLUCELVAX QUADRIVALENT met the pre-defined success criterion defined as the lower limit of the two-sided 95% CI of absolute vaccine efficacy greater than 20%
^4 Non-Influenza Comparator: (MENVEO, meningococcal (Groups A, C, Y, and W-135) oligosaccharide diphtheria CRM197 conjugate vaccine, GlaxoSmithKline Biologicals SA); children assigned to 2 doses received saline placebo as the second dose.
Study 4: NCT03165617

14.3 Immunogenicity in Adults

Immunogenicity in adults 18 years of age and older was evaluated in clinical Study 6, a randomized, active controlled, multicenter study conducted in Poland during the 2004-05 Northern Hemisphere influenza season. In this study, immunogenicity was assessed 3 weeks after vaccination in 2640 subjects who received either FLUCELVAX (N=1322) or the egg-based trivalent influenza comparator, AGRIFLU (N=1318). Among the overall study population enrolled, 59% were female, 100% of subjects were Caucasian, and the mean age was 43.6 years.

In study 6, non-inferiority of FLUCELVAX to AGRIFLU was demonstrated for HI antibody responses to all three strains for both post-vaccination geometric mean titre (GMT) ratios and seroconversion rates. Success for non-inferiority of the GMT ratio was defined as the lower limit of the two-sided 95% CI for GMT ratio (FLUCELVAX / AGRIFLU) was >0.67; and success for non-inferiority of seroconversion rate was defined as the lower limit of the two-sided 95% CI for the difference between the seroconversion rates (FLUCELVAX – AGRIFLU) was >-10%) (Table 9).

Table 9: Non-inferiority Analysis of FLUCELVAX to a US-Licensed Comparator in Adults 18 through 49 Years and 50 through 64 Years of Age (Study 6^1)
 | Ratio or Difference (95% CI) FLUCELVAX Versus Comparator^2
 | A/H1N1 | A/H3N2 | B
Subjects 18 through 49 Years: N FLUCELVAX=478; N comparator=472
GMTs ratio^3,4 (FLUCELVAX / AGRIFLU) | 0.96 (0.81, 1.13) | 0.98 (0.87, 1.11) | 1.07 (0.93, 1.23)
Difference in Seroconversion Rates^4,5,6 (FLUCELVAX – AGRIFLU) | 2% (-4, 8) | 2% (-5, 8) | 5% (1, 10)
Subjects 50 through 64 Years: N FLUCELVAX=340; N comparator=365
GMTs ratio^3,4 (FLUCELVAX / AGRIFLU) | 0.96 (0.79, 1.16) | 0.87 (0.74, 1.02) | 1.23 (1.02, 1.48)
Difference in Seroconversion Rates^4,5,6 (FLUCELVAX – AGRIFLU) | 1% (-6, 8) | -2% (-9, 5) | 3% (-4, 9)
^1 NCT00492063
^2 AGRIFLU (Influenza Virus Vaccine)
^3 Non inferiority was demonstrated if the lower limit of the two-sided 95% confidence interval (CI) for geometric mean titer (GMT) ratio (FLUCELVAX/AGRIFLU) was >0.67.
^4 Egg derived antigen hemagglutination inhibition (HI) assay results
^5 Rates of seroconversion = percentage of subjects with either a pre-vaccination HI titer < 1:10 and a post-vaccination HI titer ≥ 1:40 or a pre-vaccination HI titer ≥ 1:10 and at least a four-fold rise in post-vaccination HI antibody titer
^6 Non inferiority was demonstrated if the lower limit of two-sided 95% confidence interval (CI) for difference in percentages of subjects with seroconversion (FLUCELVAX – AGRIFLU) was >-10%.

Non-inferiority of FLUCELVAX to AGRIFLU was demonstrated for HI antibody responses to all three strains for both post-vaccination GMT ratios and seroconversion rates. Success for non-inferiority of the GMT ratio was defined as the lower limit of the two-sided 95% CI for the GMT ratio (FLUCELVAX / AGRIFLU) >0.67; and success for non-inferiority of seroconversion rate was defined as the lower limit of the two-sided 95% CI for the difference between the seroconversion rates (FLUCELVAX – AGRIFLU) >-10%) (Table 10).

Table 10: Non-inferiority Analysis of FLUCELVAX to a US-Licensed Comparator in Adults 65 Years of Age and Older (Study 6^1)
 | Ratio or Difference (95% CI) FLUCELVAX Versus Comparator^2 (N FLUCELVAX=504; N comparator=481)
 | A/H1N1 | A/H3N2 | B
GMTs ratio^3,4 (FLUCELVAX / AGRIFLU) | 1.06 (0.92, 1.22) | 0.97 (0.84, 1.12) | 1.28 (1.1, 1.48)
Difference in Seroconversion Rates^4,5,6 (FLUCELVAX – AGRIFLU) | -1% (-7, 6) | 3% (-2, 9) | 7% (1, 12)
^1 NCT 00492063
^2 AGRIFLU (Influenza Virus Vaccine)
^3 Non inferiority was demonstrated if the lower limit of the two-sided 95% confidence interval (CI) for geometric mean titer (GMT) ratio (FLUCELVAX/AGRIFLU) was >0.67.
^4 Egg derived antigen hemagglutination inhibition (HI) assay results
^5 Rates of seroconversion = percentage of subjects with either a pre-vaccination HI titer < 1:10 and a post-vaccination HI titer ≥ 1:40 or a pre-vaccination HI titer ≥ 1:10 and at least a four-fold rise in post-vaccination HI antibody titer
^6 Non inferiority was demonstrated if the lower limit of the two-sided 95% confidence interval (CI) for difference in percentages of subjects with seroconversion (FLUCELVAX – AGRIFLU) was >-10%.

14.4 Immunogenicity in Children

Immunogenicity in children 6 months through 3 years of age was evaluated in a randomized, observer-blind, multicenter study conducted in the US (Study 1). In this study, subjects received FLUCELVAX QUADRIVALENT or a US-licensed comparator quadrivalent influenza vaccine (FLUCELVAX QUADRIVALENT N=1597, Comparator QUADRIVALENT (QIV) N=805). In the per protocol set, the mean age of subjects who received FLUCELVAX QUADRIVALENT was 29 months; 49% of subjects were female and 67% of subjects were Caucasian, 27% were Black and < 1% were Asian, Hawaiian or other Pacific Islander and American Indian or Alaska Native. Twenty six percent of subjects were of Hispanic origin. The immune response to each of the vaccine antigens was assessed 28 days after last vaccination.

The immunogenicity endpoints were geometric mean antibody titers (GMTs) and percentage of subjects who achieved seroconversion, defined as a pre-vaccination HI or microneutralization (MN) titer of < 1:10 with a post-vaccination titer ≥ 1:40 or with a pre-vaccination HI or MN titer ≥ 1:10 and a minimum 4-fold increase in serum antibody titer. GMTs and seroconversion rates were measured by hemagglutination inhibition (HI) assay for A/H1N1, B/Yamagata and B/Victoria strains and by microneutralization (MN) assay for the A/H3N2 strain.

FLUCELVAX QUADRIVALENT was noninferior to the Comparator QIV. Noninferiority was established for all 4 influenza strains as assessed by ratios of GMTs and the differences in the percentages of subjects achieving seroconversion at 4 weeks following vaccination.

The noninferiority data observed are summarized in Table 11.

Table 11: Noninferiority^1 of FLUCELVAX QUADRIVALENT Relative to Comparator QIV in Children 6 Months through 3 Years of Age – Per-Protocol Analysis Set^2 (Study 1)
 |  | FLUCELVAX QUADRIVALENT | Comparator QIV | Vaccine Group Ratio | Vaccine Group Difference
A/H1N1* |  | N=1092 | N=575
A/H1N1* | GMT (95% CI) | 78.0 (70.75, 86.03) | 57.3 (50.76, 64.63) | 0.73 (0.65, 0.84) | -
A/H1N1* | Seroconversion Rate^3 (95% CI) | 58.24% (55.25, 61.19) | 46.78% (42.64, 50.96) | - | -11.46 (-16.45, -6.42)
A/H3N2# |  | N = 1078 | N = 572
A/H3N2# | GMT (95% CI) | 23.1 (21.21, 25.12) | 23.9 (21.57, 26.57) | 1.04 (0.93, 1.16) | -
A/H3N2# | Seroconversion Rate^3 (95% CI) | 27.64% (24.99, 30.42) | 30.77% (27.01, 34.73) | - | 3.13 (-1.44, 7.81)
B/Yamagata* |  | N = 1092 | N = 575
B/Yamagata* | GMT (95% CI) | 35.6 (32.93, 38.58) | 26.0 (23.54, 28.63) | 0.73 (0.66, 0.81) | -
B/Yamagata* | Seroconversion Rate^3 (95% CI) | 46.52% (43.53, 49.53) | 31.65% (27.87, 35.63) | - | -14.87 (-19.61, -9.98)
B/Victoria* |  | N = 1092 | N = 575
B/Victoria* | GMT (95% CI) | 22.4 (20.70, 24.19) | 19.6 (17.81, 21.58) | 0.88 (0.79, 0.97) | -
B/Victoria* | Seroconversion Rate^3 (95% CI) | 30.31% (27.60, 33.13) | 24.35% (20.89, 28.07) | - | -5.96 (-10.33, -1.44)
Abbreviations: GMT = geometric mean titer. CI = confidence interval.
Assays: GMTs and seroconversion rates were measured by hemagglutination inhibition (HI)* assay for A/H1N1, B/Yamagata and B/Victoria strains and by microneutralization (MN)# assay for the A/H3N2 strain, using cell-derived target viruses. The MN assay was used for A/H3N2 as circulating strains indicated a reduced ability to agglutinate red blood cells. FLUCELVAX QUADRIVALENT was noninferior to the Comparator QIV irrespective of the assay used. HI assay data for A/H3N2: GMT (95%CI) for FLUCELVAX QUADRIVALENT (N=1089) = 288.1 (261.46, 317.54), Comparator QIV (N=575) = 227.6 (201.87, 256.58), Vaccine group ratio (95%CI) = 0.79 (0.69, 0.90), Seroconversion rate (95%CI) for FLUCELVAX QUADRIVALENT (N=1089) = 72.27% (69.51,74.91), Comparator QIV (N=575) = 64.52% (60.46, 68.44), Vaccine Group Difference (95%CI) = -7.75% (-12.51, -3.06).
Success criteria: The upper bound of the two-sided 95% confidence interval (CI) on the ratio of the GMTs (calculated as GMT US-licensed comparator QIV divided by GMT FLUCELVAX QUADRIVALENT) does not exceed 1.5. The upper bound of the two-sided 95% CI on the difference between the seroconversion rates (calculated as Seroconversion rate US-licensed comparator QIV minus Seroconversion rate FLUCELVAX QUADRIVALENT) does not exceed 10%.
^1 Analyses are performed on data for Day 29 for previously vaccinated subjects and Day 57 for not previously vaccinated subjects.
^2 Per protocol set: All participants in Full Analysis Set, immunogenicity population, who have correctly received the assigned vaccine, have no major protocol deviations leading to exclusion as defined prior to unblinding/ analysis and are not excluded due to other reasons defined prior to unblinding or analysis.
^3 Seroconversion rate = percentage of subjects with either a pre-vaccination titer < 1:10 and post-vaccination titer ≥ 1:40 or with a pre-vaccination titer ≥ 1:10 and a minimum 4-fold increase in post-vaccination antibody titer
Study 1: NCT 04074928

15 REFERENCES

1. Lasky T, Terracciano GJ, Magder L, et al. The Guillain-Barré syndrome and the 1992-1993 and 1993-1994 influenza vaccines. N Engl J Med 1998; 339(25):1797-1802.
2. Hannoun C, Megas F, Piercy J. Immunogenicity and protective efficacy of influenza vaccination. Virus Res 2004; 103:133-138.
3. Hobson D, Curry RL, Beare A, et al. The role of serum hemagglutinin-inhibiting antibody in protection against challenge infection with influenza A2 and B viruses. J Hyg Camb 1972; 767-777.

16 HOW SUPPLIED/STORAGE AND HANDLING

FLUCELVAX product presentations are listed in Table 12 below:

Table 12: FLUCELVAX Product Presentations
Presentation | Carton NDC Number | Components
Pre-filled Syringe | 70461-655-03 | 0.5 mL single dose pre-filled syringe, package of 10 syringes per carton [NDC 70461-655-04]
Multi-dose Vial | 70461-555-10 | 5 mL multi-dose vial, individually packaged in a carton [NDC 70461-555-11]

Store this product refrigerated at 2°C to 8°C (36ºF to 46ºF). Between uses, return the multi-dose vial to the recommended storage conditions. Do not freeze. Protect from light. Do not use after the expiration date.

17 PATIENT COUNSELING INFORMATION

Inform vaccine recipients of the potential benefits and risks of immunization with FLUCELVAX.

Educate vaccine recipients regarding the potential side effects; clinicians should emphasize that (1) FLUCELVAX contains non-infectious particles and cannot cause influenza and (2) FLUCELVAX is intended to provide protection against illness due to influenza viruses only and cannot provide protection against other respiratory illnesses.

Instruct vaccine recipients to report adverse reactions to their healthcare provider.

Provide vaccine recipients with the Vaccine Information Statements which are required by the National Childhood Vaccine Injury Act of 1986. These materials are available free of charge at the Centers for Disease Control and Prevention (CDC) website (www.cdc.gov/vaccines).

Inform vaccine recipients that annual vaccination is recommended.

FLUCELVAX and FLUCELVAX QUADRIVALENT are registered trademarks of Seqirus UK Limited or its affiliates.

Manufactured by: Seqirus Inc. Holly Springs, NC 27540, USA

US License No. 2049

Distributed by: Seqirus USA Inc. 25 Deforest Avenue, Summit, NJ 07901, USA

1-855-358-8966

Principal Display Panel – 0.5 mL Carton Label

NDC 70461-655-03

For use in persons 6 months of age and older

For Intramuscular Use

Ten 0.5 mL, single-dose, pre-filled syringes

Rx Only

Influenza Vaccine
FLUCELVAX®

2025 - 2026 FORMULA

Seqirus™

Principal Display Panel – 0.5 mL Syringe Label

Influenza Vaccine
FLUCELVAX®

2025 - 2026 Formula

0.5 mL dose

Rx Only

FOR IM USE

For 6 months of age
and older

NDC 70461-655-04

Principal Display Panel – 5 mL Carton Label

NDC 70461-555-10

5 mL Multi-dose Vial Rx Only

For use in persons 6 months of age and older

For Intramuscular Use

Influenza Vaccine
FLUCELVAX®

2025 - 2026 FORMULA

Seqirus™

Principal Display Panel – 5 mL Vial Label

NDC 70461-555-11

Influenza Vaccine
FLUCELVAX®

2025 - 2026 Formula

5 mL Multi-dose Vial

FOR IM USE Rx Only

For use in persons 6 months of
age and older.